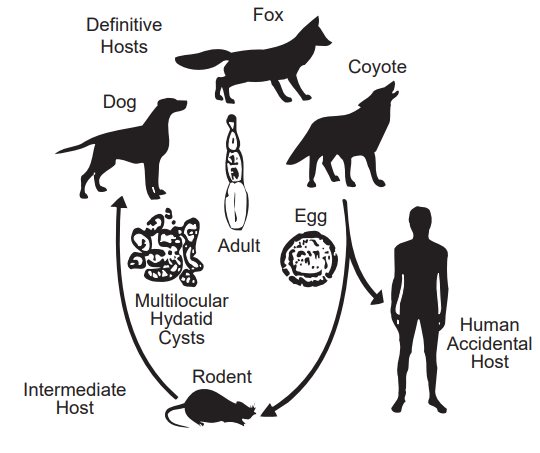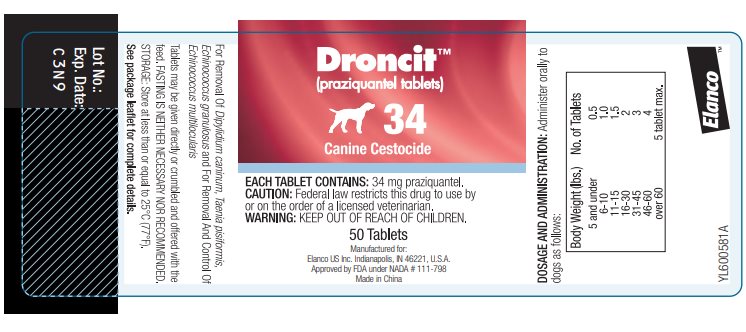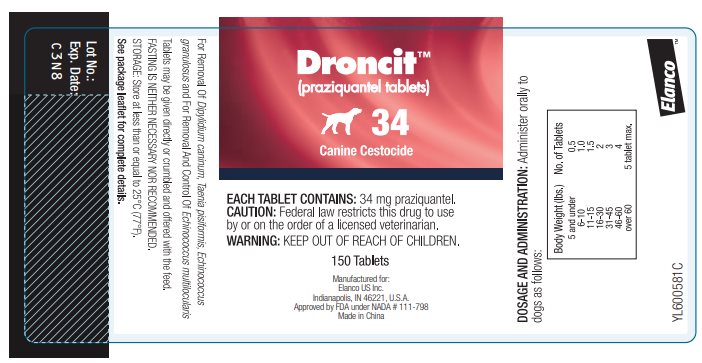 DRUG LABEL: Droncit Canine Cestocide
NDC: 58198-0033 | Form: TABLET
Manufacturer: Elanco US Inc.
Category: animal | Type: PRESCRIPTION ANIMAL DRUG LABEL
Date: 20260223

ACTIVE INGREDIENTS: PRAZIQUANTEL 34 mg/1 1

Elanco
DroncitTM
(praziquantel tablets)
34 Canine Cestocide

CAUTION: Federal law restricts this drug to use by or on the order of a licensed veterinarian.

Each tablet contains 34 mg praziquantel.

DESCRIPTION:

Droncit (praziquantel tablets) 34 Canine Cestocide are sized for easy oral administration to either adult dogs or puppies. The tablets may be crumbled and mixed with the feed.

INDICATIONS:

Droncit (praziquantel tablets) 34 Canine Cestocide are indicated for the removal of the following canine cestodes: Dipylidium caninum, Taenia pisiformis, Echinococcus granulosus and for the removal and control of Echinococcus multilocularis.

CONTRAINDICATIONS:

There are no known contraindications to the use of praziquantel in dogs.

ACTION:

Droncit (praziquantel tablets) is absorbed, metabolized in the liver and excreted in the bile. Upon entering the digestive tract from the bile, cestocidal activity is exhibited.^1 Following exposure to praziquantel, the tapeworm loses its ability to resist digestion by the mammalian host. Because of this, whole tapeworms, including the scolex, are very rarely passed after administration of praziquantel. In many instances only disintegrated and partially digested pieces of tapeworms will be seen in the stool. The majority of tapeworms are digested and are not found in the feces.

USE DIRECTIONS:

Droncit (praziquantel tablets) 34 Canine Cestocide may be administered directly per os or crumbled and mixed with the feed. The recommended dosage of praziquantel varies according to body weight. Smaller animals require a relatively larger dosage because of their higher metabolic rate. The optimum dose for each individual animal will be achieved by utilizing the following dosage schedule:

Dogs and Puppies*
5 lbs. and under | ½ tablet
6-10 lbs. | 1 tablet
11-15 lbs. | 1 ½ tablets
16-30 lbs. | 2 tablets
31-45 lbs. | 3 tablets
46-60 lbs. | 4 tablets
Over 60 lbs. | 5 tablets max
* Not intended for use in puppies less than 4 weeks of age.

FASTING:

The recommended dosage of praziquantel is not affected by the presence or absence of food in the gastrointestinal tract, therefore, FASTING IS NEITHER NECESSARY NOR RECOMMENDED.

RETREATMENT:

For those animals living where reinfections are likely to occur, clients should be instructed in the steps to optimize prevention, otherwise, retreatment may be necessary. This is true in cases of Dipylidium caninum where reinfection is almost certain to occur if fleas are not removed from the animal and its environment. In addition, for control of Echinococcus multilocularis, a program of regular treatment every 21 to 26 days may be indicated (see E. multilocularis section below).

ECHINOCOCCUS MULTILOCULARIS:

Echinococcus multilocularis is a tapeworm species ordinarily considered to be found in wild canids, including foxes, coyotes and wolves. The parasite has also been identified in domestic dogs and cats and potentially is a serious public health concern by involving humans as accidental intermediate hosts.

The life cycle of the parasite is based on a predator-prey relationship, as depicted.

The adult tapeworm is small (1-4 mm) and resides in the intestinal tract of the definitive host (wild or domestic canids). Eggs from the adult tapeworm are shed in the feces of the infected canid. Rodents such as mice and voles serve as the intermediate host for E. multilocularis. Eggs ingested by rodents develop in the liver, lungs and other organs to form multilocular cysts. The life cycle is completed after a canid consumes a rodent infected with cysts. After ingestion of an infected rodent, larvae contained within the cyst develop into adult tapeworms in the intestinal tract of the canid. Eggs may begin to be passed in the feces of the canid approximately 28 days later.

This parasite poses a serious public health problem because of the possibility for human involvement in the life cycle. If eggs shed by an infected canid are accidentally ingested, a highly pathogenic condition (Alveolar Hydatid Disease) results from development of the cyst stage in humans.

The original geographic distribution of E. multilocularis was primarily confined to northern areas of North America. Current evidence indicates migration of the parasite well into the continental United States.^2,3

Domestic dogs living in E. multilocularis endemic areas that roam freely with the opportunity to catch wild rodents are at risk for infection. Pet owners should be advised on how to minimize this risk. Proper restraint of roaming dogs should be encouraged, along with regular treatment with Droncit (praziquantel tablets) following the established dosage schedule (above) and the precautions indicated below.

Additional information on the life cycle and epidemiology of this parasite is available in veterinary parasitology texts.^4,5

DIAGNOSIS:

Diagnosis of E. multilocularis in canids is difficult. The adult tapeworm produces no clinical signs of infection. Tapeworm segments (proglottids) are usually not observed in the feces. E. multilocularis eggs, observed using microscopic fecal examination procedures, are similar in appearance to the common taeniid species of canids such as Taenia pisiformis.

Assistance in the diagnosis of E. multilocularis may be available from a state veterinary diagnostic laboratory. Additional information regarding areas where E. multilocularis is suspected or has been confirmed may be obtained from area veterinary schools or the Centers for Disease Control in Atlanta, GA.

TREATMENT:

Dogs infected with E. multilocularis should be treated to prevent exposure of humans to infective eggs and to reduce perpetuation of the parasite’s life cycle.

The dosage of Droncit (praziquantel tablets) for removal of E. multilocularis is the same as that indicated for the removal of the other tapeworm species listed on the label. Laboratory efficacy studies have demonstrated the recommended dosage is 100% efficacious for removal of this tapeworm.

Under condition of continual exposure to wild rodents, retreatment of the dog at 21-26 day intervals is recommended to prevent the shedding of infectious eggs.

PRECAUTIONS:

Strict hygienic precautions should be taken when handling dogs or feces suspected of harboring E. multilocularis. Infected dogs treated for the first time with Droncit (praziquantel tablets) and dogs treated at intervals greater than 28 days may shed eggs in the feces after treatment. The animal should be held in the clinic during this interval and all feces should be incinerated or autoclaved. If these procedures are not possible, the eggs can be destroyed by soaking the feces in a sodium hypochlorite (bleach) solution of 3.75% or greater.^6 All areas where the animal was maintained or in contact with should be thoroughly cleaned with sodium hypochlorite and allowed to dry completely before reuse.

ANIMAL SAFETY:

The safety index has been derived from controlled safety evaluations, clinical trials and prior approved use in foreign countries. Dosages of 5 times the labeled rate at 14 day intervals to dogs as young as 4 weeks did not produce clinical signs of toxicity. No significant clinical chemistry, hematological, cholinesterase, or histopathological changes occurred. Symptoms of gross overdosage include vomition, salivation, diarrhea and depression.

PREGNANCY:

Droncit (praziquantel tablets) has been tested in breeding and pregnant dogs. No adverse effects were noted.

ADVERSE REACTIONS:

Seven instances (3.2%) of either vomiting, anorexia, lethargy or diarrhea were reported during the field trials in which 218 dogs were administered Droncit (praziquantel tablets) 34 canine cestocide. The investigators rated these as non-significant.

CONTACT INFORMATION:

For product questions, to report adverse reactions, or for a copy of the Safety Data Sheet (SDS), call Elanco Product & Veterinary Support at 888-545-5973. For additional information about reporting adverse drug experiences for animal drugs, contact FDA at 1-888-FDA-VETS or http://www.fda.gov/reportanimalae.

WARNING:

Keep out of reach of children. Not for human use.

STORAGE:

Store at less than or equal to 25ºC (77ºF)

HOW SUPPLIED:

Bottle of 50 and 150 scored tablets.

Each scored tablet contains 34 mg praziquantel.

— 50 Tablets

— 150 Tablets

REFERENCES:

1. Andrews, P. Pharmacokinetic Studies with Droncit in Animals Using a Biological Assay. Veterinary Medical Review 2/76: 154-165.
2. Hildreth, M.B., Johnson, M.D. and Kozacos, K.R. 1991. A Zoonosis of Increasing Concern in the United States. Compendium for Cont Ed 13(5): 727-740.
3. Lieby, P.D., Carney, W.P., and Woods, C.E. 1970. Studies on Sylvatic Echinococcosis. Ill. Host Occurrence and Geographic Distribution of Echinococcus multilocularis in the North Central United States. J Parasit 56(6): 1141-1150.
4. Georgi, J.R. and Georgi M.E. 1990. Parasitology for Veterinarians.W.B. Saunders Co. 118-138.
5. Soulsby, E.J.L. 1982. Helminths, Arthropods and Protozoa of Domesticated Animals. 7th Edition. Lea & Febigir 118-138.
6. Craig, P.S. and McPharson, C.N.L. 1988. Sodium Hypochlorite as an Ovicide for Echinococcus. Ann Trop Med and Parasit 82(2): 211-213.

Manufactured for:
Elanco US Inc.
Indianapolis, IN 46221, U.S.A.

Droncit, Elanco and the diagonal bar logo are trademarks of Elanco or its affiliates.

© 2025 Elanco or its affiliates

Approved by FDA under NADA # 111-798

PA600581X

Revised: November 2025

Elanco™

Principal Display Panel

DroncitTM

(praziquantel tablets)

34

Canine Cestocide

EACH TABLET CONTAINS: 34 mg praziquantel.

CAUTION: Federal law restricts this drug to use by
or on the order of a licensed veterinarian.

WARNING: KEEP OUT OF REACH OF CHILDREN.

50 Tablets

Manufactured for:
Elanco US Inc. Indianapolis, IN 46221, U.S.A.
Approved by FDA under NADA # 111-798
Made in China

DroncitTM

(praziquantel tablets)

34

Canine Cestocide

EACH TABLET CONTAINS: 34 mg praziquantel.

CAUTION: Federal law restricts this drug to use
by or on the order of a licensed veterinarian.

WARNING: KEEP OUT OF REACH OF CHILDREN.

150 Tablets

Manufactured for:
Elanco US Inc.
Indianapolis, IN 46221, U.S.A.
Approved by FDA under NADA # 111-798
Made in China